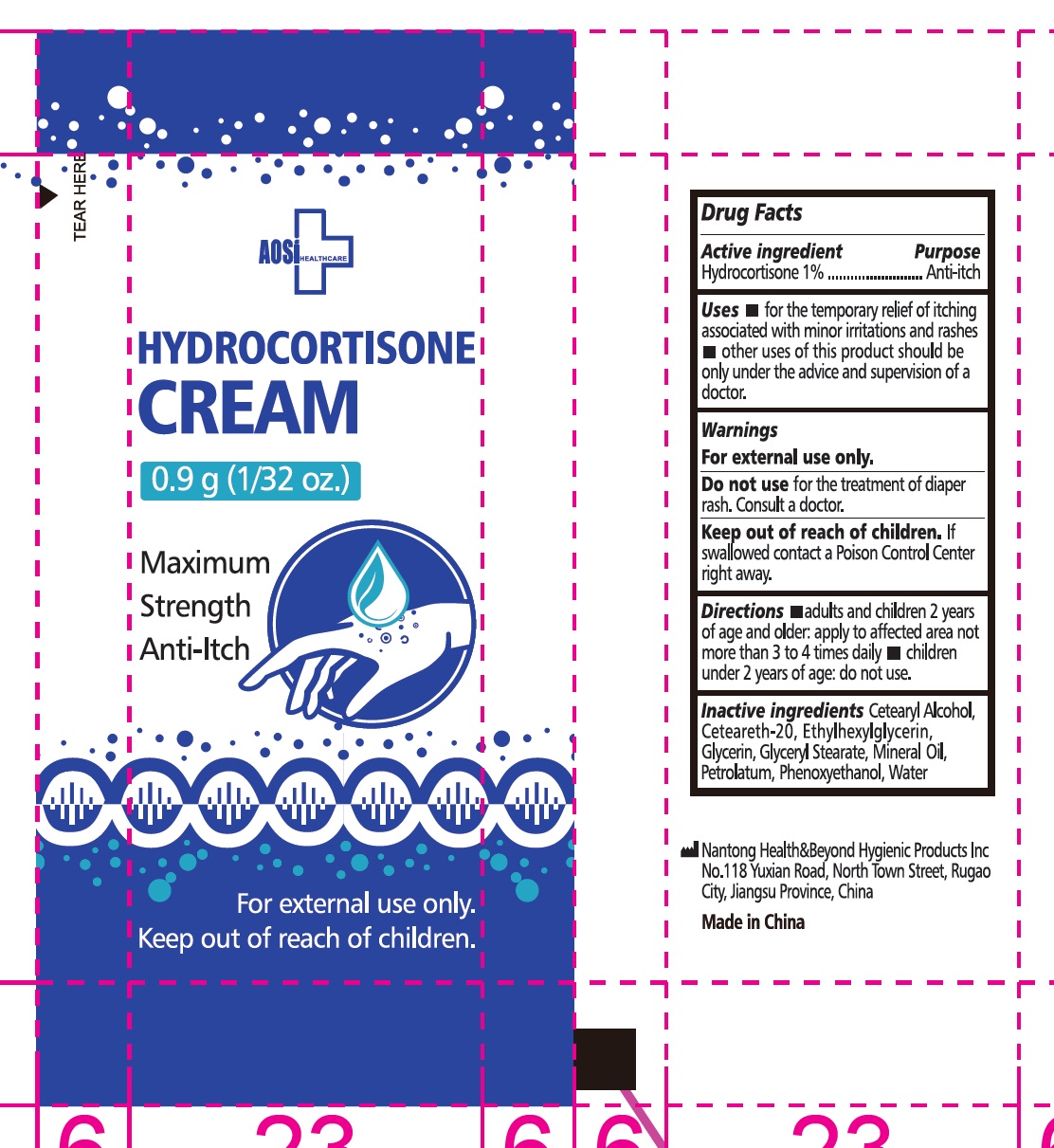 DRUG LABEL: AOSI HEALTHCARE
NDC: 43473-054 | Form: CREAM
Manufacturer: Nantong Health & Beyond Hygienic Products Inc.
Category: otc | Type: HUMAN OTC DRUG LABEL
Date: 20240925

ACTIVE INGREDIENTS: HYDROCORTISONE 1 g/100 g
INACTIVE INGREDIENTS: WATER; GLYCERIN; POLYOXYL 20 CETOSTEARYL ETHER; CETOSTEARYL ALCOHOL; ETHYLHEXYLGLYCERIN; MINERAL OIL; PETROLATUM; PHENOXYETHANOL; GLYCERYL STEARATE SE

43473-054 AOSI Healthcare Hydrocortison

Active ingredient

Hydrocortisone 1%

Purpose Anti-itch

Uses

- for temorary relief of itching associated with minor irritations and rashes
- other uses of this product should be only under the advice and supervision of a doctor

Warnings

For external use only.

Do not use

- for the treatment of diaper rash. Consult a doctor

Keep out of reach of children. If swallowed, contact a Poison Control Center right away.

Directions

- adults and children 2 years of age and older: apply to affected area not more than 3 to 4 times daily
- children under 2 years of age: do not use

Inactive ingredients

cetearyl alcohol, ceteareth-20, ethylhexylglycerin, glycerin, glyceryl stearate, mineral oil, petrolactum, phenoxyethanol, water